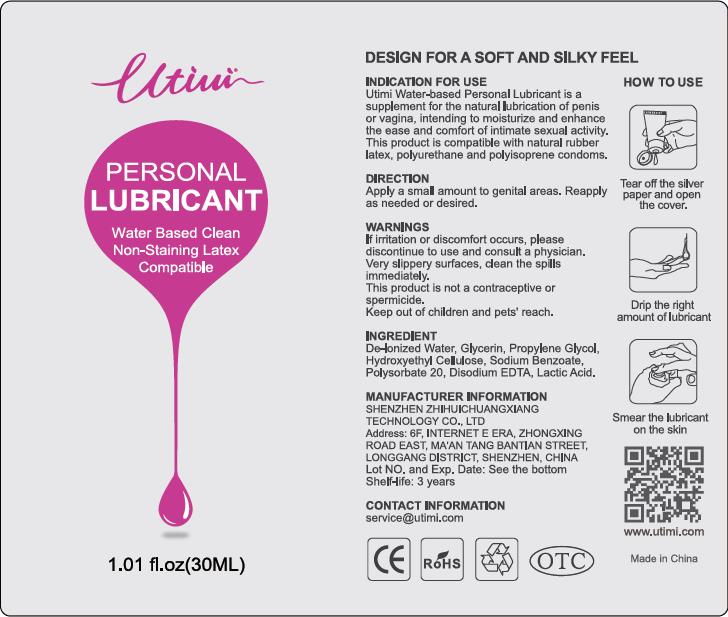 DRUG LABEL: UTIMI Water Based Personal Lubricant
NDC: 73000-225 | Form: LOTION
Manufacturer: Shenzhen ZhiHuiChuangXiang Technology Co., Ltd
Category: otc | Type: HUMAN OTC DRUG LABEL
Date: 20190327

ACTIVE INGREDIENTS: HYDROXYETHYL CELLULOSE (140 CPS AT 5%) 0.381 g/30 mL
INACTIVE INGREDIENTS: EDETATE DISODIUM ANHYDROUS 0.027 mL/30 mL; SODIUM BENZOATE 0.3 mL/30 mL; WATER 25.008 mL/30 mL; POLYSORBATE 20 0.075 mL/30 mL; GLYCERIN 2.538 mL/30 mL; PROPYLENE GLYCOL 1.665 mL/30 mL; LACTIC ACID, DL- 0.006 mL/30 mL

Water Based Personal Lubricant, UTIMI, 30mL

Active ingredient

Hydroxyethyl Cellulose

Inactive ingredient

De-lonized Water
Glycerin
Propylene Glycol
Sodium Benzoate
Polysorbate 20
Disodium EDTA
Lactic Acid

Purpose

Utimi Personal Lubricant is a water-based lubricant for penile or vaginal application, intended to moisturize and enhance the ease and comfort of intimate sexual activity as well as supplement for the body's natural lubrication.

This product is compatible with natural rubber latex, polyurethane and polyisoprene condoms.

When using

Virginal / Anal dryness and/or intimate sexual activity.

This product is not a contraceptive and does not contain a spermicide.

Do not use when wound or skin infection.

It should be cautiously used if you are kind of allergic constitution or you have inflammation.
Do not use if quality seal on the opening of the container is broken or missing.
Do not use if tamper-evident seal is removed or broken.

Stop use

If irritation or discomfort occurs, discontinue the use and consult a physician.
Very slippery on surfaces, clean spills immediately.

Ask doctor

If irritation or discomfort occurs, discontinue the use and consult a physician.

Ask doctor/pharmacist when you current use other drugs.

Keep out of reach of children and away from eyes and ears.

Questions

Please contact us when you have any questions.

Pregnancy or breast feeding

Pregnant or breast feeding women shall follow doctor advice.

Indications & usage

This is a water-based lubricant for penile or vaginal application, intended to moisturize and enhance the ease and comfort of intimate sexual activity as well as supplement for the body's natural lubrication.

Apply a small amount to genital areas. Reapply as needed or desired.

Dosage & administration

Apply a small amount to genital areas. Reapply as needed or desired.

Dosage forms & strengths

The lubricant is like oil form.

One capsule (0.9g lubricant and 0.3g gelatin coated) once time.

The active ingredient strength is 0.324g.

Warnings

If irritation or discomfort occurs, pleas discontinue to use and consult a physician.

Very slippery surfaces, clean the spills immediately.

This product is not a contraceptive or spermicide.

Keep out of children and pets' reach.

Package label. Principal display panel

As attached.